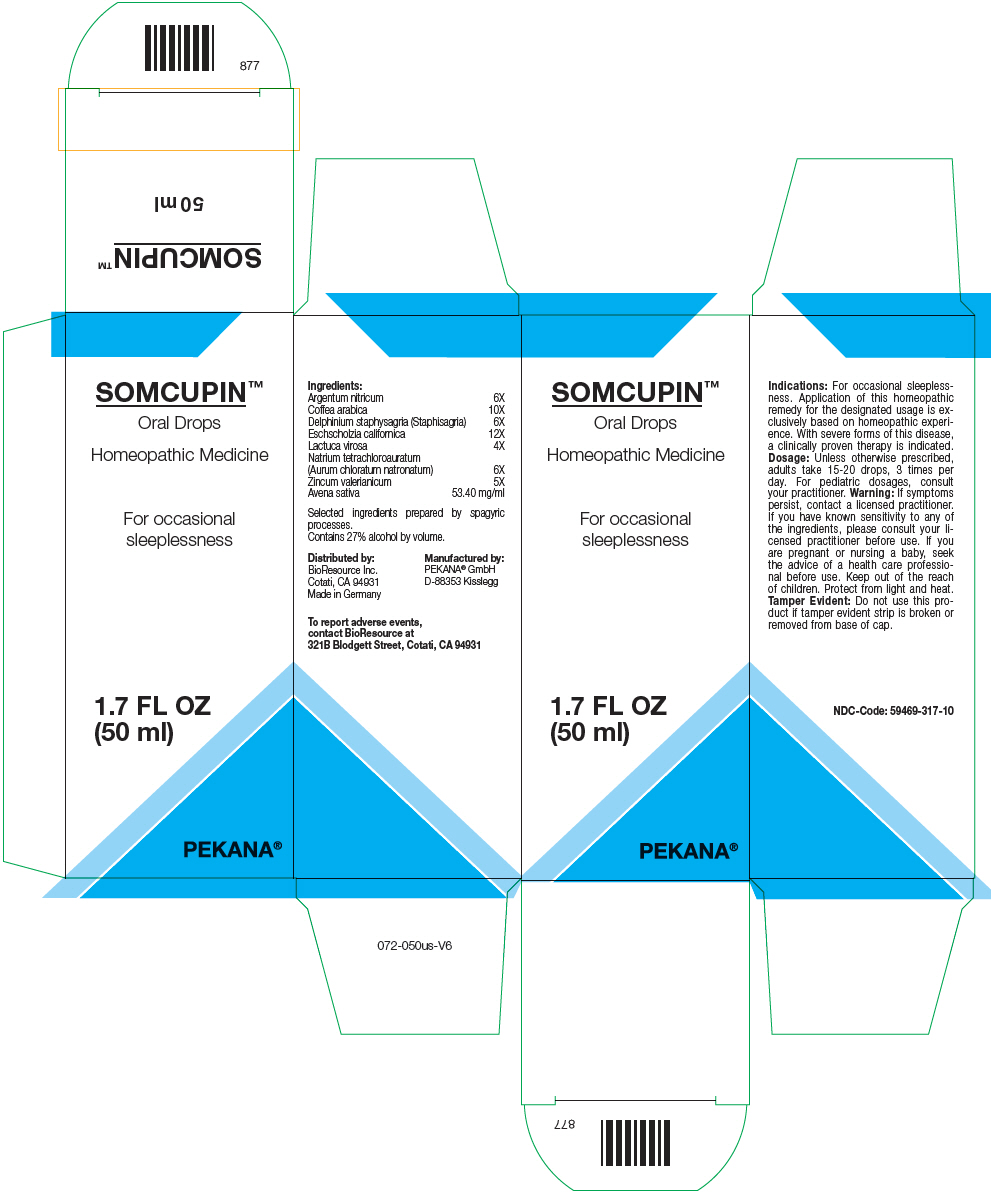 DRUG LABEL: SOMCUPIN
NDC: 59469-317 | Form: SOLUTION/ DROPS
Manufacturer: PEKANA Naturheilmittel GmbH
Category: homeopathic | Type: HUMAN OTC DRUG LABEL
Date: 20230111

ACTIVE INGREDIENTS: SILVER NITRATE 6 [hp_X]/50 mL; SODIUM TETRACHLOROAURATE 6 [hp_X]/50 mL; ARABICA COFFEE BEAN 10 [hp_X]/50 mL; DELPHINIUM STAPHISAGRIA SEED 6 [hp_X]/50 mL; LACTUCA VIROSA WHOLE 4 [hp_X]/50 mL; ZINC VALERATE DIHYDRATE 5 [hp_X]/50 mL; ESCHSCHOLZIA CALIFORNICA FLOWERING TOP 12 [hp_X]/50 mL; AVENA SATIVA FLOWERING TOP 2670 mg/50 mL
INACTIVE INGREDIENTS: WATER; ALCOHOL

SOMCUPIN™

ACTIVE INGREDIENT

Ingredients:
Argentum nitricum | 6X
Coffea arabica | 10X
Delphinium staphysagria (Staphisagria) | 6X
Eschscholzia californica | 12X
Lactuca virosa | 4X
Natrium tetrachloroauratum (Aurum chloratum natronatum) | 6X
Zincum valerianicum | 5X
Avena sativa | 53.40 mg/ml

Selected ingredients prepared by spagyric processes.

INACTIVE INGREDIENT

Contains 27% alcohol by volume.

Indications

PURPOSE

For occasional sleeplessness. Application of this homeopathic remedy for the designated usage is exclusively based on homeopathic experience. With severe forms of this disease, a clinically proven therapy is indicated.

Dosage

Unless otherwise prescribed, adults take 15-20 drops, 3 times per day. For pediatric dosages, consult your practitioner.

Warning

If symptoms persist, contact a licensed practitioner. If you have known sensitivity to any of the ingredients, please consult your licensed practitioner before use. If you are pregnant or nursing a baby, seek the advice of a health care professional before use.

Keep out of the reach of children.

STORAGE AND HANDLING

Protect from light and heat.

Tamper Evident

Do not use this product if tamper evident strip is broken or removed from base of cap.

QUESTIONS

To report adverse events, contact BioResource at 321B Blodgett Street, Cotati, CA 94931

Distributed by:
BioResource Inc.
Cotati, CA 94931

Manufactured by:
PEKANA® GmbH
D-88353 Kisslegg

PRINCIPAL DISPLAY PANEL - 50 ml Bottle Box

SOMCUPIN™

Oral Drops

Homeopathic Medicine

For occasional
sleeplessness

1.7 FL OZ
(50 ml)

PEKANA®